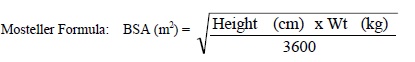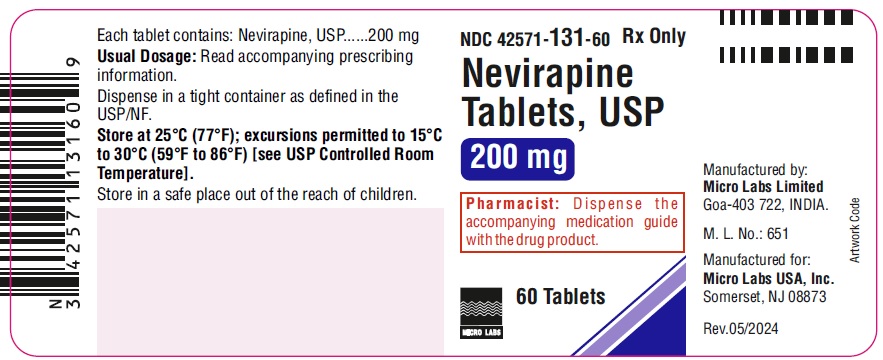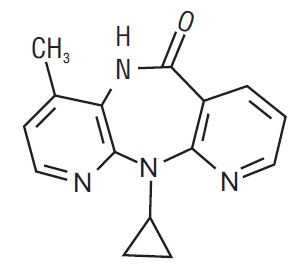 DRUG LABEL: NEVIRAPINE

NDC: 42571-131 | Form: TABLET
Manufacturer: Micro Labs Limited
Category: prescription | Type: HUMAN PRESCRIPTION DRUG LABEL
Date: 20251016

ACTIVE INGREDIENTS: NEVIRAPINE 200 mg/1 1
INACTIVE INGREDIENTS: CELLULOSE, MICROCRYSTALLINE; LACTOSE MONOHYDRATE; SILICON DIOXIDE; MAGNESIUM STEARATE; POVIDONE K25; SODIUM STARCH GLYCOLATE TYPE A POTATO

HIGHLIGHTS OF PRESCRIBING INFORMATION

These highlights do not include all the information needed to use NEVIRAPINE TABLETS safely and effectively. See full prescribing information for NEVIRAPINE TABLETS.
NEVIRAPINE tablets, for oral use
Initial U.S. Approval: 1996

WARNING: LIFE-THREATENING (INCLUDING FATAL) HEPATOTOXICITY and SKIN REACTIONS

See full prescribing information for complete boxed warning.

- Fatal and non-fatal hepatotoxicity have been reported in patients taking nevirapine. Discontinue immediately if clinical hepatitis or transaminase elevations combined with rash or other systemic symptoms occur. Do not restart nevirapine after recovery. (5.1)
- Fatal and non-fatal skin reactions, including Stevens-Johnson syndrome, toxic epidermal necrolysis, and hypersensitivity reactions, have been reported. Discontinue immediately if severe skin reactions, hypersensitivity reactions, or any rash with systemic symptoms occur. Check transaminase levels immediately for all patients who develop a rash in the first 18 weeks of treatment. Do not restart nevirapine after recovery. (5.2)
- Monitoring during the first 18 weeks of therapy is essential. Extra vigilance is warranted during the first 6 weeks of therapy, which is the period of greatest risk of these events. (5.1, 5.2)

1 INDICATIONS AND USAGE

- Nevirapine tablet is an NNRTI indicated in combination with other antiretroviral agents for the treatment of human immunodeficiency virus (HIV-1) infection in adults and pediatric patients 15 days and older. (1)

Limitations of Use:

Based on serious and life-threatening hepatotoxicity observed in controlled and uncontrolled trials, nevirapine tablet is not recommended to be initiated, unless the benefit outweighs the risk, in:

- adult females with CD4^+cell counts greater than 250 cells/mm^3
- adult males with CD4^+cell counts greater than 400 cells/mm^3(1, 5.1)

2 DOSAGE AND ADMINISTRATION

- The 14-day lead-in period must be strictly followed; it has been demonstrated to reduce the frequency of rash. (2.4, 5.2)
- If any patient experiences rash during the 14-day lead-in period, do not increase dose until the rash has resolved. Do not continue the lead-in dosing regimen beyond 28 days. (2.4)
- If dosing is interrupted for greater than 7 days, restart 14-day lead-in dosing. (2.4)

 | Adults (≥16 yrs) | Pediatric Patients* (≥15 days)
First 14 days | 200 mg once daily | 150 mg/m^2once daily
After 14 days | 200 mg twice daily | 150 mg/m^2twice daily

*Total daily dose should not exceed 400 mg for any patient.

3 DOSAGE FORMS AND STRENGTHS

- 200 mg tablets (3)

4 CONTRAINDICATIONS

- Patients with moderate or severe (Child-Pugh Class B or C, respectively) hepatic impairment. (4, 5.1, 8.7)
- Use as part of occupational and non-occupational post-exposure prophylaxis (PEP) regimens, an unapproved use. (4, 5.1)

5 WARNINGS AND PRECAUTIONS

- Monitor patients for immune reconstitution syndrome and fat redistribution. (5.5, 5.6)

6 ADVERSE REACTIONS

- The most common adverse reaction is rash. In adults, the incidence of rash is 15% versus 6% with placebo, with Grade 3/4 rash occurring in 2% of subjects. (6.1)
- In pediatric subjects the incidence of rash (all causality) was 21%. (6.1)

To report SUSPECTED ADVERSE REACTIONS, contact Micro Labs USA, Inc. at 1-855-839-8195 or FDA at 1-800-FDA-1088 or www.fda.gov/medwatch.

7 DRUG INTERACTIONS

Co-administration of nevirapine can alter the concentrations of other drugs and other drugs may alter the concentration of nevirapine. The potential for drug interactions must be considered prior to and during therapy. (5.4, 7, 12.3)

8 USE IN SPECIFIC POPULATIONS

- Lactation: Women infected with HIV-1 should be instructed not to breastfeed due to the potential for HIV-1 transmission. (8.2)
- No dose adjustment is required for patients with renal impairment with a creatinine clearance greater than or equal to 20 mL per min. Patients on dialysis receive an additional dose of 200 mg following each dialysis treatment. (2.4, 8.6)
- Monitor patients with hepatic fibrosis or cirrhosis carefully for evidence of drug-induced toxicity. Do not administer nevirapine to patients with Child-Pugh B or C. (5.1, 8.7)

FULL PRESCRIBING INFORMATION

WARNING: LIFE-THREATENING (INCLUDING FATAL) HEPATOTOXICITY and SKIN REACTIONS

HEPATOTOXICITY:

Severe, life-threatening, and in some cases fatal hepatotoxicity, particularly in the first 18 weeks, has been reported in patients treated with nevirapine. In some cases, patients presented with non-specific prodromal signs or symptoms of hepatitis and progressed to hepatic failure. These events are often associated with rash. Female gender and higher CD4^+cell counts at initiation of therapy place patients at increased risk; women with CD4+ cell counts greater than 250 cells/mm^3, including pregnant women receiving nevirapine in combination with other antiretrovirals for the treatment of HIV-1 infection, are at the greatest risk. However, hepatotoxicity associated with nevirapine use can occur in both genders, all CD4^+cell counts and at any time during treatment. Hepatic failure has also been reported in patients without HIV taking nevirapine for post-exposure prophylaxis (PEP). Use of nevirapine for occupational and non-occupational PEP is contraindicated [see Contraindications (4)] . Patients with signs or symptoms of hepatitis, or with increased transaminases combined with rash or other systemic symptoms, must discontinue nevirapine and seek medical evaluation immediately [see Warnings and Precautions (5.1)] .

SKIN REACTIONS:

Severe, life-threatening skin reactions, including fatal cases, have occurred in patients treated with nevirapine. These have included cases of Stevens-Johnson syndrome, toxic epidermal necrolysis, and hypersensitivity reactions characterized by rash, constitutional findings, and organ dysfunction. Patients developing signs or symptoms of severe skin reactions or hypersensitivity reactions must discontinue nevirapine and seek medical evaluation immediately. Transaminase levels should be checked immediately for all patients who develop a rash in the first 18 weeks of treatment. The 14-day lead-in period with nevirapine 200 mg daily dosing has been observed to decrease the incidence of rash and must be followed [see Warnings and Precautions (5.2)] .

MONITORING FOR HEPATOTOXICITY AND SKIN REACTIONS:

Patients must be monitored intensively during the first 18 weeks of therapy with nevirapine to detect potentially life-threatening hepatotoxicity or skin reactions. Extra vigilance is warranted during the first 6 weeks of therapy, which is the period of greatest risk of these events. Do not restart nevirapine following clinical hepatitis, or transaminase elevations combined with rash or other systemic symptoms, or following severe skin rash or hypersensitivity reactions. In some cases, hepatic injury has progressed despite discontinuation of treatment.

1 INDICATIONS AND USAGE

Nevirapine tablet is indicated in combination with other antiretroviral agents for the treatment of human immunodeficiency virus (HIV-1) infection in adults and pediatric patients 15 days and older [see Clinical Studies (14.1, 14.2)] .

Limitations of Use:

Based on serious and life-threatening hepatotoxicity observed in controlled and uncontrolled trials, nevirapine tablet is not recommended to be initiated, unless the benefit outweighs the risk, in:

- adult females with CD4^+cell counts greater than 250 cells/mm^3or
- adult males with CD4^+cell counts greater than 400 cells/mm^3 [see Warnings and Precautions (5.1)] .

2 DOSAGE AND ADMINISTRATION

2.1 Adult Patients

The recommended dose for nevirapine is one 200 mg tablet daily for the first 14 days, followed by one 200 mg tablet twice daily, in combination with other antiretroviral agents. The 14-day lead-in period with nevirapine 200 mg daily dosing must be strictly followed as the lead-in period has been observed to decrease the incidence of rash [see Dosage and Administration (2.4)and Warnings and Precautions (5.2)] . If rash persists beyond the 14-day lead-in period, do not dose escalate to 200 mg twice daily. The 200 mg once-daily dosing regimen should not be continued beyond 28 days, at which point, an alternative regimen should be sought. For concomitantly administered antiretroviral therapy, the manufacturer’s recommended dosage and monitoring should be followed.

2.2 Pediatric Patients

The recommended oral dose for pediatric patients 15 days and older is 150 mg/m^2once daily for 14 days followed by 150 mg/m^2twice daily thereafter. The total daily dose should not exceed 400 mg for any patient.

2.3 Monitoring of Patients

Intensive clinical and laboratory monitoring, including liver enzyme tests, is essential at baseline and during the first 18 weeks of treatment with nevirapine. The optimal frequency of monitoring during this period has not been established. Some experts recommend clinical and laboratory monitoring more often than once per month, and in particular, would include monitoring of liver enzyme tests at baseline, prior to dose escalation, and at two weeks post-dose escalation. After the initial 18-week period, frequent clinical and laboratory monitoring should continue throughout nevirapine treatment [see Warnings and Precautions (5)] . In some cases, hepatic injury has progressed despite discontinuation of treatment.

2.4 Dosage Adjustment

Patients with Rash

Discontinue nevirapine if a patient experiences severe rash or any rash accompanied by constitutional findings [see Warnings and Precautions (5.2)] . Do not increase nevirapine dose if a patient experiences mild to moderate rash without constitutional symptoms during the 14-day lead-in period of 200 mg/day (150 mg/m^2/day in pediatric patients) until the rash has resolved [see Warnings and Precautions (5.2)] . The total duration of the once daily lead-in dosing period should not exceed 28 days at which point an alternative regimen should be sought.

Patients with Hepatic Events

If a clinical (symptomatic) hepatic event occurs, permanently discontinue nevirapine. Do not restart nevirapine after recovery [see Warnings and Precautions (5.1)] .

Patients with Dose Interruption

For patients who interrupt nevirapine dosing for more than 7 days, restart the recommended dosing, using one 200 mg tablet daily (150 mg/m^2/day in pediatric patients) for the first 14 days (lead-in) followed by one 200 mg tablet twice daily (150 mg/m^2twice daily for pediatric patients).

Patients with Renal Impairment

Patients with CrCl greater than or equal to 20 mL per min do not require an adjustment in nevirapine dosing. The pharmacokinetics of nevirapine have not been evaluated in patients with CrCl less than 20 mL per min. An additional 200 mg dose of nevirapine following each dialysis treatment is indicated in patients requiring dialysis. Nevirapine metabolites may accumulate in patients receiving dialysis; however, the clinical significance of this accumulation is not known [see Clinical Pharmacology (12.3)] .

3 DOSAGE FORMS AND STRENGTHS

Tablets: Nevirapine tablets USP, 200 mg are White to off-white, oval, biconvex tablet, marked on one side as “I” and “11” separated with a breakline and plain on other side.

4 CONTRAINDICATIONS

Nevirapine is contraindicated:

- in patients with moderate or severe (Child-Pugh Class B or C, respectively) hepatic impairment [see Warnings and Precautions (5.1)and Use in Specific Populations (8.7)].
- for use as part of occupational and non-occupational post-exposure prophylaxis (PEP) regimens [see Warnings and Precautions (5.1)] .

5 WARNINGS AND PRECAUTIONS

5.1 Hepatotoxicity and Hepatic Impairment

Severe, life-threatening, and in some cases fatal hepatotoxicity, including fulminant and cholestatic hepatitis, hepatic necrosis and hepatic failure, have been reported in patients treated with nevirapine. In controlled clinical trials, symptomatic hepatic events regardless of severity occurred in 4% (range 0% to 11%) of subjects who received nevirapine and 1% of subjects in control groups.

The risk of symptomatic hepatic events regardless of severity was greatest in the first 6 weeks of therapy. The risk continued to be greater in the nevirapine groups compared to controls through 18 weeks of treatment. However, hepatic events may occur at any time during treatment. In some cases, subjects presented with non-specific, prodromal signs or symptoms of fatigue, malaise, anorexia, nausea, jaundice, liver tenderness or hepatomegaly, with or without initially abnormal serum transaminase levels. Rash was observed in approximately half of the subjects with symptomatic hepatic adverse events. Fever and flu-like symptoms accompanied some of these hepatic events. Some events, particularly those with rash and other symptoms, have progressed to hepatic failure with transaminase elevation, with or without hyperbilirubinemia, hepatic encephalopathy, prolonged partial thromboplastin time, or eosinophilia. Rhabdomyolysis has been observed in some patients experiencing skin and/or liver reactions associated with nevirapine use. Hepatitis/hepatic failure may be associated with signs of hypersensitivity which can include severe rash or rash accompanied by fever, general malaise, fatigue, muscle or joint aches, blisters, oral lesions, conjunctivitis, facial edema, eosinophilia, granulocytopenia, lymphadenopathy, or renal dysfunction. Patients with signs or symptoms of hepatitis must be advised to discontinue nevirapine and immediately seek medical evaluation, which should include liver enzyme tests.

The first 18 weeks of therapy with nevirapine are a critical period during which intensive clinical and laboratory monitoring of patients is required to detect potentially life-threatening hepatic events. The optimal frequency of monitoring during this time period has not been established. Some experts recommend clinical and laboratory monitoring more often than once per month, and in particular, include monitoring of liver enzyme tests at baseline, prior to dose escalation and at two weeks post-dose escalation. After the initial 18-week period, frequent clinical and laboratory monitoring should continue throughout nevirapine treatment.

Transaminases should be checked immediately if a patient experiences signs or symptoms suggestive of hepatitis and/or hypersensitivity reaction. Transaminases should also be checked immediately for all patients who develop a rash in the first 18 weeks of treatment. Physicians and patients should be vigilant for the appearance of signs or symptoms of hepatitis, such as fatigue, malaise, anorexia, nausea, jaundice, bilirubinuria, acholic stools, liver tenderness or hepatomegaly. The diagnosis of hepatotoxicity should be considered in this setting, even if transaminases are initially normal or alternative diagnoses are possible [see Dosage and Administration (2.3)] .

If clinical hepatitis or transaminase elevations combined with rash or other systemic symptoms occur, permanently discontinue nevirapine. Do not restart nevirapine after recovery. In some cases, hepatic injury progresses despite discontinuation of treatment.

The patients at greatest risk of hepatic events, including potentially fatal events, are women with high CD4^+cell counts. In general, during the first 6 weeks of treatment, women have a 3-fold higher risk than men for symptomatic, often rash-associated, hepatic events (6% versus 2%), and patients with higher CD4^+cell counts at initiation of nevirapine therapy are at higher risk for symptomatic hepatic events with nevirapine. In a retrospective review, women with CD4^+cell counts greater than 250 cells/mm^3had a 12-fold higher risk of symptomatic hepatic adverse events compared to women with CD4^+cell counts less than 250 cells/mm^3(11% versus 1%). An increased risk was observed in men with CD4^+cell counts greater than 400 cells/mm^3(6% versus 1% for men with CD4^+cell counts less than 400 cells/mm^3). However, all patients, regardless of gender, CD4^+cell count, or antiretroviral treatment history, should be monitored for hepatotoxicity since symptomatic hepatic adverse events have been reported at all CD4^+cell counts. Co-infection with hepatitis B or C and/or increased transaminase elevations at the start of therapy with nevirapine are associated with a greater risk of later symptomatic events (6 weeks or more after starting nevirapine) and asymptomatic increases in AST or ALT.

In addition, serious hepatotoxicity (including liver failure requiring transplantation in one instance) has been reported in HIV-1 uninfected individuals receiving multiple doses of nevirapine in the setting of post-exposure prophylaxis (PEP), an unapproved use. Use of nevirapine for occupational and non-occupational PEP is contraindicated [see Contraindications (4)] .

Increased nevirapine trough concentrations have been observed in some patients with hepatic fibrosis or cirrhosis. Therefore, carefully monitor patients with either hepatic fibrosis or cirrhosis for evidence of drug-induced toxicity. Do not administer nevirapine to patients with moderate or severe (Child-Pugh Class B or C, respectively) hepatic impairment [see Contraindications (4), Use in Specific Populations (8.7), and Clinical Pharmacology (12.3)] .

5.2 Skin Reactions

Severe and life-threatening skin reactions, including fatal cases, have been reported, occurring most frequently during the first 6 weeks of therapy. These have included cases of Stevens-Johnson syndrome, toxic epidermal necrolysis, and hypersensitivity reactions characterized by rash, constitutional findings, and organ dysfunction including hepatic failure. Rhabdomyolysis has been observed in some patients experiencing skin and/or liver reactions associated with nevirapine use. In controlled clinical trials, Grade 3 and 4 rashes were reported during the first 6 weeks in 2% of nevirapine recipients compared to less than 1% of placebo subjects.

Patients developing signs or symptoms of severe skin reactions or hypersensitivity reactions (including, but not limited to, severe rash or rash accompanied by fever, general malaise, fatigue, muscle or joint aches, blisters, oral lesions, conjunctivitis, facial edema, and/or hepatitis, eosinophilia, granulocytopenia, lymphadenopathy, and renal dysfunction) must permanently discontinue nevirapine and seek medical evaluation immediately. Do not restart nevirapine following severe skin rash, skin rash combined with increased transaminases or other symptoms, or hypersensitivity reaction.

The first 18 weeks of therapy with nevirapine are a critical period during which intensive clinical and laboratory monitoring of patients is required to detect potentially life-threatening skin reactions. The optimal frequency of monitoring during this time period has not been established. Some experts recommend clinical and laboratory monitoring more often than once per month, and in particular, include monitoring of liver enzyme tests at baseline, prior to dose escalation and at two weeks post-dose escalation. After the initial 18-week period, frequent clinical and laboratory monitoring should continue throughout nevirapine treatment. In addition, the 14-day lead-in period with nevirapine 200 mg daily dosing has been demonstrated to reduce the frequency of rash [see Dosage and Administration (2.1)] .

If patients present with a suspected nevirapine-associated rash, measure transaminases immediately. Permanently discontinue nevirapine in patients with rash-associated transaminase elevations [see Warnings and Precautions (5.1)] .

Therapy with nevirapine must be initiated with a 14-day lead-in period of 200 mg per day (150 mg/m^2per day in pediatric patients), which has been shown to reduce the frequency of rash. Discontinue nevirapine if a patient experiences severe rash or any rash accompanied by constitutional findings. Do not increase nevirapine dose to a patient experiencing a mild to moderate rash without constitutional symptoms during the 14-day lead-in period of 200 mg per day (150 mg/m^2/day in pediatric patients) until the rash has resolved .The total duration of the once-daily lead-in dosing period must not exceed 28 days at which point an alternative regimen should be sought [see Dosage and Administration (2.4)] . Patients must be monitored closely if isolated rash of any severity occurs. Delay in stopping nevirapine treatment after the onset of rash may result in a more serious reaction.

Women appear to be at higher risk than men of developing rash with nevirapine.

In a clinical trial, concomitant prednisone use (40 mg per day for the first 14 days of nevirapine administration) was associated with an increase in incidence and severity of rash during the first 6 weeks of nevirapine therapy. Therefore, use of prednisone to prevent nevirapine-associated rash is not recommended.

5.3 Resistance

Nevirapine must not be used as a single agent to treat HIV-1 or added on as a sole agent to a failing regimen. Resistant virus emerges rapidly when nevirapine is administered as monotherapy. The choice of new antiretroviral agents to be used in combination with nevirapine should take into consideration the potential for cross resistance. When discontinuing an antiretroviral regimen containing nevirapine, the long half-life of nevirapine should be taken into account; if antiretrovirals with shorter half-lives than nevirapine are stopped concurrently, low plasma concentrations of nevirapine alone may persist for a week or longer and virus resistance may subsequently develop [see Microbiology (12.4)] .

5.4 Drug Interactions

See Table 4 for listings of established and potential drug interactions [see Drug Interactions (7)] .

Concomitant use of St. John's wort (Hypericum perforatum) or St. John's wort-containing products and nevirapine is not recommended. Co-administration of St. John’s wort with non-nucleoside reverse transcriptase inhibitors (NNRTIs), including nevirapine, is expected to substantially decrease NNRTI concentrations and may result in sub-optimal levels of nevirapine and lead to loss of virologic response and possible resistance to nevirapine or to the class of NNRTIs. Co-administration of nevirapine and efavirenz is not recommended as this combination has been associated with an increase in adverse reactions and no improvement in efficacy.

5.5 Immune Reconstitution Syndrome

Immune reconstitution syndrome has been reported in patients treated with combination antiretroviral therapy, including nevirapine. During the initial phase of combination antiretroviral treatment, patients whose immune system responds may develop an inflammatory response to indolent or residual opportunistic infections (such as Mycobacterium aviuminfection, cytomegalovirus, Pneumocystis jirovecipneumonia, or tuberculosis), which may necessitate further evaluation and treatment.

Autoimmune disorders (such as Graves’ disease, polymyositis, and Guillain-Barré syndrome) have also been reported to occur in the setting of immune reconstitution, however, the time to onset is more variable, and can occur many months after initiation of treatment.

5.6 Fat Redistribution

Redistribution/accumulation of body fat including central obesity, dorsocervical fat enlargement (buffalo hump), peripheral wasting, facial wasting, breast enlargement, and “cushingoid appearance” have been observed in patients receiving antiretroviral therapy. The mechanism and long-term consequences of these events are currently unknown. A causal relationship has not been established.

6 ADVERSE REACTIONS

6.1 Clinical Trials Experience

Because clinical trials are conducted under widely varying conditions, adverse reaction rates observed in the clinical trials of a drug cannot be directly compared to rates in the clinical trials of another drug and may not reflect the rates observed in clinical practice.

Clinical Trial Experience in Adult Patients

The most serious adverse reactions associated with nevirapine are hepatitis, hepatic failure, Stevens-Johnson syndrome, toxic epidermal necrolysis, and hypersensitivity reactions. Hepatitis/hepatic failure may be isolated or associated with signs of hypersensitivity which may include severe rash or rash accompanied by fever, general malaise, fatigue, muscle or joint aches, blisters, oral lesions, conjunctivitis, facial edema, eosinophilia, granulocytopenia, lymphadenopathy, or renal dysfunction [see Boxed Warning and Warnings and Precautions (5.1, 5.2)] .

Hepatic Reaction

In controlled clinical trials, symptomatic hepatic events regardless of severity occurred in 4% (range 0% to 11%) of subjects who received nevirapine and 1% of subjects in control groups. Female gender and higher CD4^+cell counts (greater than 250 cells/mm^3in women and greater than 400 cells/mm^3in men) place patients at increased risk of these events [see Boxed Warning and Warnings and Precautions (5.1)] .

Asymptomatic transaminase elevations (AST or ALT greater than 5X ULN) were observed in 6% (range 0% to 9%) of subjects who received nevirapine and 6% of subjects in control groups. Co-infection with hepatitis B or C and/or increased transaminase elevations at the start of therapy with nevirapine are associated with a greater risk of later symptomatic events (6 weeks or more after starting nevirapine) and asymptomatic increases in AST or ALT.

Liver enzyme abnormalities (AST, ALT, GGT) were observed more frequently in subjects receiving nevirapine than in controls (see Table 3).

Skin Reaction

The most common clinical toxicity of nevirapine is rash, which can be severe or life-threatening [see Boxed Warning and Warnings and Precautions (5.2)] . Rash occurs most frequently within the first 6 weeks of therapy. Rashes are usually mild to moderate, maculopapular erythematous cutaneous eruptions, with or without pruritus, located on the trunk, face and extremities. In controlled clinical trials (Trials 1037, 1038, 1046, and 1090), Grade 1 and 2 rashes were reported in 13% of subjects receiving nevirapine compared to 6% receiving placebo during the first 6 weeks of therapy. Grade 3 and 4 rashes were reported in 2% of nevirapine recipients compared to less than 1% of subjects receiving placebo. Women tend to be at higher risk for development of nevirapine-associated rash [see Boxed Warning and Warnings and Precautions (5.2)] .

Treatment-related, adverse experiences of moderate or severe intensity observed in greater than 2% of subjects receiving nevirapine in placebo-controlled trials are shown in Table 2.

Table 2 Percentage of Subjects with Moderate or Severe Drug-Related Events in Adult Placebo-Controlled Trials

 | Trial 1090^1 |  | Trials 1037, 1038, 1046^2
 | Nevirapine (n=1121) | Placebo (n=1128) | Nevirapine (n=253) | Placebo (n=203)
Median exposure (weeks) | 58 | 52 | 28 | 28
Any adverse event | 15% | 11% | 32% | 13%
Rash | 5 | 2 | 7 | 2
Nausea | 1 | 1 | 9 | 4
Granulocytopenia | 2 | 3 | <1 | 0
Headache | 1 | <1 | 4 | 1
Fatigue | <1 | <1 | 5 | 4
Diarrhea | <1 | 1 | 2 | 1
Abdominal pain | <1 | <1 | 2 | 0
Myalgia | <1 | 0 | 1 | 2

^1Background therapy included 3TC for all subjects and combinations of NRTIs and PIs. Subjects had CD4^+cell counts less than 200 cells/mm^3.

^2Background therapy included ZDV and ZDV+ddI; nevirapine monotherapy was administered in some subjects. Subjects had CD4^+cell count greater than or equal to 200 cells/mm^3.

Laboratory Abnormalities

Liver enzyme test abnormalities (AST, ALT) were observed more frequently in subjects receiving nevirapine than in controls (Table 3). Asymptomatic elevations in GGT occur frequently but are not a contraindication to continue nevirapine therapy in the absence of elevations in other liver enzyme tests. Other laboratory abnormalities (bilirubin, anemia, neutropenia, thrombocytopenia) were observed with similar frequencies in clinical trials comparing nevirapine and control regimens (see Table 3).

Table 3 Percentage of Adult Subjects with Laboratory Abnormalities

 | Trial 1090^1 |  | Trials 1037, 1038, 1046^2
 | Nevirapine | Placebo | Nevirapine | Placebo
Laboratory Abnormality | (n=1121) | (n=1128) | (n=253) | (n=203)
Blood Chemistry
SGPT (ALT) >250 U/L | 5 | 4 | 14 | 4
SGOT (AST) >250 U/L | 4 | 3 | 8 | 2
Bilirubin >2.5 mg/dL | 2 | 2 | 2 | 2
Hematology
Hemoglobin <8.0 g/dL | 3 | 4 | 0 | 0
Platelets <50,000/mm^3 | 1 | 1 | <1 | 2
Neutrophils <750/mm^3 | 13 | 14 | 4 | 1

^1Background therapy included 3TC for all subjects and combinations of NRTIs and PIs. Subjects had CD4^+cell counts less than 200 cells/mm^3.

^2Background therapy included ZDV and ZDV+ddI; nevirapine monotherapy was administered in some subjects. Subjects had CD4^+cell count greater than or equal to 200 cells/mm^3.

Clinical Trial Experience in Pediatric Patients

Adverse events were assessed in BI Trial 1100.1032 (ACTG 245), a double-blind, placebo-controlled trial of nevirapine (n=305) in which pediatric subjects received combination treatment with nevirapine. In this trial two subjects were reported to experience Stevens-Johnson syndrome or Stevens-Johnson/toxic epidermal necrolysis transition syndrome. Safety was also assessed in trial BI 1100.882 (ACTG 180), an open-label trial of nevirapine (n=37) in which subjects were followed for a mean duration of 33.9 months (range: 6.8 months to 5.3 years, including long-term follow-up in 29 of these subjects in trial BI 1100.892). The most frequently reported adverse events related to nevirapine in pediatric subjects were similar to those observed in adults, with the exception of granulocytopenia, which was more commonly observed in children receiving both zidovudine and nevirapine. Cases of allergic reaction, including one case of anaphylaxis, were also reported.

The safety of nevirapine was also examined in BI Trial 1100.1368, an open-label, randomized clinical trial performed in South Africa in which 123 HIV-1 infected treatment-naïve subjects between 3 months and 16 years of age received combination treatment with lamivudine and zidovudine for 48 weeks [see Use in Specific Populations (8.4) and Clinical Pharmacology (12.3)] . Rash (all causality) was reported in 21% of the subjects, 4 (3%) of whom discontinued drug due to rash. All 4 subjects experienced the rash early in the course of therapy (less than 4 weeks) and resolved upon nevirapine discontinuation. Other clinically important adverse events (all causality) include neutropenia (9%), anemia (7%), and hepatotoxicity (2%) [see Use in Specific Populations (8.4) and Clinical Studies (14.2)] .

Safety information on use of nevirapine in combination therapy in pediatric subjects 2 weeks to less than 3 months of age was assessed in 36 subjects from the BI 1100.1222 (PACTG 356) trial. No unexpected safety findings were observed although granulocytopenia was reported more frequently in this age group compared to the older pediatric age groups and adults.

6.2 Postmarketing Experience

In addition to the adverse events identified during clinical trials, the following adverse reactions have been identified during post-approval use of nevirapine. Because these reactions are reported voluntarily from a population of uncertain size, it is not always possible to reliably estimate their frequency or establish a causal relationship to drug exposure.

Body as a Whole:fever, somnolence, drug withdrawal [see Drug Interactions (7)] , redistribution/accumulation of body fat [see Warnings and Precautions (5.6)]

Gastrointestinal:vomiting

Liver and Biliary:jaundice, fulminant and cholestatic hepatitis, hepatic necrosis, hepatic failure

Hematology:anemia, eosinophilia, neutropenia

Investigations:decreased serum phosphorus

Musculoskeletal:arthralgia, rhabdomyolysis associated with skin and/or liver reactions

Neurologic:paraesthesia

Skin and Appendages:Allergic reactions including anaphylaxis, angioedema, bullous eruptions, ulcerative stomatitis and urticaria have all been reported. In addition, hypersensitivity syndrome and hypersensitivity reactions with rash associated with constitutional findings such as fever, blistering, oral lesions, conjunctivitis, facial edema, muscle or joint aches, general malaise, fatigue, or significant hepatic abnormalities, drug reaction with eosinophilia and systemic symptoms (DRESS) [see Warnings and Precautions (5.1)] plus one or more of the following: hepatitis, eosinophilia, granulocytopenia, lymphadenopathy, and/or renal dysfunction have been reported.

In post-marketing surveillance anemia has been more commonly observed in children although development of anemia due to concomitant medication use cannot be ruled out.

7 DRUG INTERACTIONS

Nevirapine is principally metabolized by the liver via the cytochrome P450 isoenzymes, 3A and 2B6. Nevirapine is known to be an inducer of these enzymes. As a result, drugs that are metabolized by these enzyme systems may have lower than expected plasma levels when co-administered with nevirapine.

The specific pharmacokinetic changes that occur with co-administration of nevirapine and other drugs are listed in Clinical Pharmacology, Table 5. Clinical comments about possible dosage modifications based on established drug interactions are listed in Table 4. The data in Tables 4 and 5 are based on the results of drug interaction trials conducted in HIV-1 seropositive subjects unless otherwise indicated. In addition to established drug interactions, there may be potential pharmacokinetic interactions between nevirapine and other drug classes that are metabolized by the cytochrome P450 system. These potential drug interactions are also listed in Table 4. Although specific drug interaction trials in HIV-1 seropositive subjects have not been conducted for some classes of drugs listed in Table 4, additional clinical monitoring may be warranted when co-administering these drugs.

The in vitrointeraction between nevirapine and the antithrombotic agent warfarin is complex. As a result, when giving these drugs concomitantly, plasma warfarin levels may change with the potential for increases in coagulation time. When warfarin is co-administered with nevirapine, anticoagulation levels should be monitored frequently.

Table 4 Established and Potential Drug Interactions: Use with Caution, Alteration in Dose or Regimen May Be Needed Due to Drug Interaction Established Drug Interactions: See Clinical Pharmacology (12.3), Table 5 for Magnitude of Interaction.

Drug Name | Effect on Concentration of Nevirapine or Concomitant Drug | Clinical Comment
HIV Antiviral Agents: Protease Inhibitors (PIs)
Atazanavir/Ritonavir* | ↓Atazanavir ↑Nevirapine | Do not co-administer nevirapine with atazanavir because nevirapine substantially decreases atazanavir exposure and there is a potential risk for nevirapine-associated toxicity due to increased nevirapine exposures.
Fosamprenavir* Fosamprenavir/Ritonavir* | ↓Amprenavir ↑Nevirapine ↓Amprenavir ↑Nevirapine | Co-administration of nevirapine and fosamprenavir without ritonavir is not recommended. No dosing adjustments are required when nevirapine is co-administered with 700/100 mg of fosamprenavir/ritonavir twice daily. The combination of nevirapine administered with fosamprenavir/ritonavir once daily has not been studied.
Indinavir* | ↓Indinavir | The appropriate doses of this combination of indinavir and nevirapine with respect to efficacy and safety have not been established.
Lopinavir/Ritonavir* | ↓Lopinavir | Dosing in adult patients: A dose adjustment of lopinavir/ritonavir to 500/125 mg tablets twice daily or 533/133 mg (6.5 mL) oral solution twice daily is recommended when used in combination with nevirapine. Neither lopinavir/ritonavir tablets nor oral solution should be administered once daily in combination with nevirapine. Dosing in pediatric patients: Please refer to the Kaletra®prescribing information for dosing recommendations based on body surface area and body weight. Neither lopinavir/ritonavir tablets nor oral solution should be administered once daily in combination with nevirapine.
Nelfinavir* | ↓Nelfinavir M8 Metabolite ↓Nelfinavir Cmin | The appropriate doses of the combination of nevirapine and nelfinavir with respect to safety and efficacy have not been established.
Saquinavir/Ritonavir | The interaction between nevirapine and saquinavir/ritonavir has not been evaluated | The appropriate doses of the combination of nevirapine and saquinavir/ritonavir with respect to safety and efficacy have not been established.
HIV Antiviral Agents: Non-Nucleoside Reverse Transcriptase Inhibitors (NNRTIs)
Efavirenz* Etravirine Rilpivirine | ↓Efavirenz | The appropriate doses of these combinations with respect to safety and efficacy have not been established. Plasma concentrations may be altered. Nevirapine should not be co-administered with another NNRTI as this combination has not been shown to be beneficial.
Other Agents
Analgesics: Methadone* | ↓Methadone | Methadone levels were decreased; increased dosages may be required to prevent symptoms of opiate withdrawal. Methadone-maintained patients beginning nevirapine therapy should be monitored for evidence of withdrawal and methadone dose should be adjusted accordingly.
Antiarrhythmics: Amiodarone, disopyramide, lidocaine | Plasma concentrations may be decreased. | Appropriate doses for this combination have not been established.
Antibiotics: Clarithromycin* Rifabutin* Rifampin* | ↓Clarithromycin ↑14-OH clarithromycin ↑Rifabutin ↓Nevirapine | Clarithromycin exposure was significantly decreased by nevirapine; however, 14-OH metabolite concentrations were increased. Because clarithromycin active metabolite has reduced activity against Mycobacterium avium- intracellulare complex, overall activity against this pathogen may be altered. Alternatives to clarithromycin, such as azithromycin, should be considered. Rifabutin and its metabolite concentrations were moderately increased. Due to high intersubject variability, however, some patients may experience large increases in rifabutin exposure and may be at higher risk for rifabutin toxicity. Therefore, caution should be used in concomitant administration. Nevirapine and rifampin should not be administered concomitantly because decreases in nevirapine plasma concentrations may reduce the efficacy of the drug. Physicians needing to treat patients co-infected with tuberculosis and using a nevirapine-containing regimen may use rifabutin instead.
Anticonvulsants: Carbamazepine, clonazepam, ethosuximide | Plasma concentrations of nevirapine and the anticonvulsant may be decreased. | Use with caution and monitor virologic response and levels of anticonvulsants.
Antifungals: Fluconazole* Ketoconazole* Itraconazole | ↑Nevirapine ↓Ketoconazole ↓Itraconazole | Because of the risk of increased exposure to nevirapine, caution should be used in concomitant administration, and patients should be monitored closely for nevirapine-associated adverse events. Nevirapine and ketoconazole should not be administered concomitantly because decreases in ketoconazole plasma concentrations may reduce the efficacy of the drug. Nevirapine and itraconazole should not be administered concomitantly due to potential decreases in itraconazole plasma concentrations that may reduce efficacy of the drug.
Antithrombotics: Warfarin | Plasma concentrations may be increased. | Potential effect on anticoagulation. Monitoring of anticoagulation levels is recommended.
Calcium Channel blockers: Diltiazem, nifedipine, verapamil | Plasma concentrations may be decreased. | Appropriate doses for these combinations have not been established.
Cancer Chemotherapy:
Cyclophosphamide | Plasma concentrations may be decreased. | Appropriate doses for this combination have not been established.
Ergot Alkaloids: Ergotamine | Plasma concentrations may be decreased. | Appropriate doses for this combination have not been established.
Immunosuppressants: Cyclosporine, tacrolimus, sirolimus | Plasma concentrations may be decreased. | Appropriate doses for these combinations have not been established.
Motility Agents: Cisapride | Plasma concentrations may be decreased. | Appropriate doses for this combination have not been established.
Opiate Agonists: Fentanyl | Plasma concentrations may be decreased. | Appropriate doses for this combination have not been established.
Oral Contraceptives: Ethinyl estradiol and Norethindrone* | ↓Ethinyl Estradiol ↓Norethindrone | Despite lower ethinyl estradiol and norethindrone exposures when co-administered with nevirapine, literature reports suggest that nevirapine has no effect on pregnancy rates among HIV-infected women on combined oral contraceptives. When co-administered with nevirapine, no dose adjustment of ethinyl estradiol or norethindrone is needed when used in combination for contraception. When these oral contraceptives are used for hormonal regulation during nevirapine therapy, the therapeutic effect of the hormonal therapy should be monitored.

*The interaction between nevirapine and the drug was evaluated in a clinical study. All other drug interactions shown are predicted.

8 USE IN SPECIFIC POPULATIONS

8.1 Pregnancy

Pregnancy Exposure Registry

There is a pregnancy exposure registry that monitors pregnancy outcomes in women exposed to nevirapine during pregnancy. Healthcare providers are encouraged to register patients by calling the Antiretroviral Pregnancy Registry (APR) at 1-800-258-4263.

Risk Summary

Available data from the APR show no difference in the risk of overall major birth defects for nevirapine compared with the background rate for major birth defects of 2.7% in the U.S. reference population of the Metropolitan Atlanta Congenital Defects Program (MACDP) [see Data]. The rate of miscarriage is not reported in the APR. The estimated background rate of miscarriage in clinically recognized pregnancies in the U.S. general population is 15 to 20%. The background risk of birth defects and miscarriage for the indicated population is unknown. Methodological limitations of the APR include the use of MACDP as the external comparator group. The MACDP population is not disease-specific, evaluates women and infants from a limited geographic area, and does not include outcomes for births that occurred at <20 weeks gestation.

In literature reports, immediate-release nevirapine exposure (Cmin) can be up to 29% lower during pregnancy. However, as this reduction was not found to be clinically meaningful, dose adjustment is not necessary [see Data].

There is a risk for severe hepatic events in pregnant women exposed to nevirapine [see Clinical Considerations].In animal reproduction studies, no evidence of adverse developmental outcomes was observed following oral administration of nevirapine during organogenesis in the rat and rabbit, at systemic exposures (AUC) to nevirapine approximately equal (rats) and 50% higher (rabbits) than the exposure in humans at the recommended 400 mg daily dose [see Data].

Clinical Considerations

Maternal adverse reactions

Severe hepatic events, including fatalities, have been reported in pregnant women receiving chronic nevirapine therapy as part of combination treatment of HIV-1 infection. Regardless of pregnancy status, women with CD4^+cell counts greater than 250 cells/mm^3should not initiate nevirapine unless the benefit outweighs the risk. It is unclear if pregnancy augments the risk observed in non-pregnant women [see Warnings and Precautions (5.1)] .

Data

Human Data

Based on prospective reports to the APR of exposures to nevirapine during pregnancy resulting in live births (including over 1100 exposed in the first trimester and over 1500 exposed in the second/third trimester), the prevalence of birth defects in live births was 3.0% (95% CI: 2.1 %, 4.1%) and 3.3% (95% CI: 2.4%, 4.3%) following first and second/third trimester exposure, respectively, to nevirapine-containing regimens, compared with the background birth defect rate of 2.7% in a U.S. reference population of the MACDP.

There are several literature reports of chronic administration of immediate-release nevirapine during pregnancy, in which nevirapine pharmacokinetics were compared between pregnancy and postpartum. In these studies, the mean difference in nevirapine Cminduring pregnancy as compared to postpartum ranged from no difference to approximately 29% lower.

Animal Data

Nevirapine was administered orally to pregnant rats (at 0, 12.5, 25, and 50 mg per kg per day) and rabbits (at 0, 30, 100, and 300 mg per kg per day) through organogenesis (on gestation days 7 through 16, and 6 through 18, respectively). No adverse developmental effects were observed at doses producing systemic exposures (AUC) approximately equivalent to (rats) or approximately 50% higher (rabbits) than human exposure at the recommended daily dose. In rats, decreased fetal body weights were observed at a maternally toxic dose at an exposure approximately 50% higher than the recommended daily dose.

8.2 Lactation

Risk Summary

The Centers for Disease Control and Prevention recommend that HIV-1 infected mothers in the United States not breastfeed their infants to avoid risking postnatal transmission of HIV-1 infection. Published data report that nevirapine is present in human milk [see Data]. There are limited data on the effects of nevirapine on the breastfed infant. There is no information on the effects of nevirapine on milk production. Because of the potential for (1) HIV-1 transmission (in HIV-negative infants), (2) developing viral resistance (in HIV-positive infants), and (3) serious adverse reactions in nursing infants, mothers should not breastfeed if they are receiving nevirapine.

Data

Based on five publications, immediate-release nevirapine was excreted in breastmilk at median concentrations ranging from 4080 to 6795 ng/mL, and the median maternal breastmilk to maternal plasma concentration ratio range was 59 to 88%. Reported infant nevirapine median plasma concentrations were low, ranging from 734 to 1140 ng/mL. The estimated nevirapine dose of 704 to 682 mcg/kg/day for infants fed exclusively with breastmilk was lower than the daily recommended nevirapine dose for infants. Published literature indicates that rash and hyperbilirubinemia have been seen in infants exposed to nevirapine through breastmilk.

8.3 Females and Males of Reproductive Potential

Infertility

Limited human data are insufficient to determine the risk of infertility in humans. Based on results from animal fertility studies conducted in rats, nevirapine may reduce fertility in females of reproductive potential. It is not known if these effects on fertility are reversible [see Nonclinical Toxicology (13.1)].

8.4 Pediatric Use

The safety, pharmacokinetic profile, and virologic and immunologic responses of nevirapine have been evaluated in HIV-1 infected pediatric subjects aged 3 months to 18 years [see Adverse Reactions (6.1)and Clinical Studies (14.2)] . The safety and pharmacokinetic profile of nevirapine has been evaluated in HIV-1 infected pediatric subjects aged 15 days to less than 3 months [see Adverse Reactions (6.1)and Clinical Studies (14.2)] .

The most frequently reported adverse events related to nevirapine in pediatric subjects were similar to those observed in adults, with the exception of granulocytopenia, which was more commonly observed in children receiving both zidovudine and nevirapine [see Adverse Reactions (6.1)and Clinical Studies (14.2)] .

8.5 Geriatric Use

Clinical trials of nevirapine did not include sufficient numbers of subjects aged 65 and older to determine whether elderly subjects respond differently from younger subjects. In general, dose selection for an elderly patient should be cautious, reflecting the greater frequency of decreased hepatic, renal or cardiac function, and of concomitant disease or other drug therapy.

8.6 Renal Impairment

In subjects with renal impairment (mild, moderate or severe), there were no significant changes in the pharmacokinetics of nevirapine. Nevirapine is extensively metabolized by the liver and nevirapine metabolites are extensively eliminated by the kidney. Nevirapine metabolites may accumulate in patients receiving dialysis; however, the clinical significance of this accumulation is not known. No adjustment in nevirapine dosing is required in patients with CrCl greater than or equal to 20 mL per min. The pharmacokinetics of nevirapine have not been evaluated in patients with CrCl less than 20 mL per min. In patients undergoing chronic hemodialysis, an additional 200 mg dose following each dialysis treatment is indicated [see Dosage and Administration (2.4)and Clinical Pharmacology (12.3)] .

8.7 Hepatic Impairment

Because increased nevirapine levels and nevirapine accumulation may be observed in patients with serious liver disease, do not administer nevirapine to patients with moderate or severe (Child-Pugh Class B or C, respectively) hepatic impairment [see Contraindications (4), Warnings and Precautions (5.1),and Clinical Pharmacology (12.3)] .

10 OVERDOSAGE

There is no known antidote for nevirapine overdosage. Cases of nevirapine overdose at doses ranging from 800 to 1800 mg per day for up to 15 days have been reported. Patients have experienced events including edema, erythema nodosum, fatigue, fever, headache, insomnia, nausea, pulmonary infiltrates, rash, vertigo, vomiting, and weight decrease. All events subsided following discontinuation of nevirapine.

11 DESCRIPTION

Nevirapine tablets USP, 200 mg is the brand name for nevirapine, a non-nucleoside reverse transcriptase inhibitor (NNRTI) with activity against Human Immunodeficiency Virus Type 1 (HIV-1). Nevirapine USP is structurally a member of the dipyridodiazepinone chemical class of compounds.
The chemical name of nevirapine is 11-cyclopropyl-5, 11-dihydro-4-methyl-6H-dipyrido [3,2-b:2',3'-e][1,4] diazepin-6-one. Nevirapine USP is a white to off-white crystalline powder with the molecular weight of 266.30 and the molecular formula C15H14N4O. Nevirapine has the following structural formula:

Nevirapine tablets USP, 200 mg is for oral administration. Each tablet contains 200 mg of nevirapine anhydrous and the inactive ingredients microcrystalline cellulose, lactose monohydrate, colloidal silicon dioxide, magnesium stearate, povidone, and Sodium starch glycolate.

12 CLINICAL PHARMACOLOGY

12.1 Mechanism of Action

Nevirapine is an antiretroviral drug [see Microbiology (12.4)] .

12.3 Pharmacokinetics

Adults

Absorption and Bioavailability

Nevirapine is readily absorbed (greater than 90%) after oral administration in healthy volunteers and in adults with HIV-1 infection. Absolute bioavailability in 12 healthy adults following single-dose administration was 93 ± 9% (mean ± SD) for a 50 mg tablet and 91 ± 8% for an oral solution. Peak plasma nevirapine concentrations of 2 ± 0.4 mcg/mL (7.5 micromolar) were attained by 4 hours following a single 200 mg dose. Following multiple doses, nevirapine peak concentrations appear to increase linearly in the dose range of 200 to 400 mg/day. Steady-state trough nevirapine concentrations of 4.5 ± 1.9 mcg/mL (17 ± 7 micromolar), (n=242) were attained at 400 mg per day. Nevirapine tablets and suspension have been shown to be comparably bioavailable and interchangeable at doses up to 200 mg. When nevirapine (200 mg) was administered to 24 healthy adults (12 female, 12 male), with either a high-fat breakfast (857 kcal, 50 g fat, 53% of calories from fat) or antacid (Maalox®30 mL), the extent of nevirapine absorption (AUC) was comparable to that observed under fasting conditions. In a separate trial in HIV-1 infected subjects (n=6), nevirapine steady-state systemic exposure (AUCƮ) was not significantly altered by didanosine, which is formulated with an alkaline buffering agent. Nevirapine may be administered with or without food, antacid or didanosine.

Distribution

Nevirapine is highly lipophilic and is essentially nonionized at physiologic pH. Following intravenous administration to healthy adults, the apparent volume of distribution (Vdss) of nevirapine was 1.21 ± 0.09 L/kg, suggesting that nevirapine is widely distributed in humans. Nevirapine readily crosses the placenta and is also found in breast milk [see Use in Specific Populations (8.2)] . Nevirapine is about 60% bound to plasma proteins in the plasma concentration range of 1 to 10 mcg per mL. Nevirapine concentrations in human cerebrospinal fluid (n=6) were 45% (±5%) of the concentrations in plasma; this ratio is approximately equal to the fraction not bound to plasma protein.

Metabolism/Elimination

In vivotrials in humans and in vitrostudies with human liver microsomes have shown that nevirapine is extensively biotransformed via cytochrome P450 (oxidative) metabolism to several hydroxylated metabolites. In vitrostudies with human liver microsomes suggest that oxidative metabolism of nevirapine is mediated primarily by cytochrome P450 (CYP) isozymes from the CYP3A and CYP2B6 families, although other isozymes may have a secondary role. In a mass balance/excretion trial in eight healthy male volunteers dosed to steady state with nevirapine 200 mg given twice daily followed by a single 50 mg dose of^14C-nevirapine, approximately 91.4 ± 10.5% of the radiolabeled dose was recovered, with urine (81.3 ± 11.1%) representing the primary route of excretion compared to feces (10.1 ± 1.5%). Greater than 80% of the radioactivity in urine was made up of glucuronide conjugates of hydroxylated metabolites. Thus cytochrome P450 metabolism, glucuronide conjugation, and urinary excretion of glucuronidated metabolites represent the primary route of nevirapine biotransformation and elimination in humans. Only a small fraction (less than 5%) of the radioactivity in urine (representing less than 3% of the total dose) was made up of parent compound; therefore, renal excretion plays a minor role in elimination of the parent compound.

Nevirapine is an inducer of hepatic cytochrome P450 (CYP) metabolic enzymes 3A and 2B6. Nevirapine induces CYP3A and CYP2B6 by approximately 20 to 25%, as indicated by erythromycin breath test results and urine metabolites. Autoinduction of CYP3A and CYP2B6 mediated metabolism leads to an approximately 1.5- to 2 fold increase in the apparent oral clearance of nevirapine as treatment continues from a single dose to two-to-four weeks of dosing with 200 to 400 mg per day. Autoinduction also results in a corresponding decrease in the terminal phase half-life of nevirapine in plasma, from approximately 45 hours (single dose) to approximately 25 to 30 hours following multiple dosing with 200 to 400 mg per day.

Specific Populations

Renal Impairment

HIV-1 seronegative adults with mild (CrCl 50 to 79 mL per min; n=7), moderate (CrCl 30 to 49 mL per min; n=6), or severe (CrCl less than 30 mL per min; n=4) renal impairment received a single 200 mg dose of nevirapine in a pharmacokinetic trial. These subjects did not require dialysis. The trial included six additional subjects with renal failure requiring dialysis.

In subjects with renal impairment (mild, moderate or severe), there were no significant changes in the pharmacokinetics of nevirapine. However, subjects requiring dialysis exhibited a 44% reduction in nevirapine AUC over a one-week exposure period. There was also evidence of accumulation of nevirapine hydroxy-metabolites in plasma in subjects requiring dialysis. An additional 200 mg dose following each dialysis treatment is indicated [see Dosage and Administration (2.4)and Use in Specific Populations (8.6)] .

Hepatic Impairment

In a steady-state trial comparing 46 subjects with mild (n=17; expansion of some portal areas; Ishak Score 1 to 2), moderate (n=20; expansion of most portal areas with occasional portal-to-portal and portal-to-central bridging; Ishak Score 3 to 4), or severe (n=9; marked bridging with occasional cirrhosis without decompensation indicating Child-Pugh A; Ishak Score 5 to 6) fibrosis as a measure of hepatic impairment, the multiple dose pharmacokinetic disposition of nevirapine and its five oxidative metabolites were not altered. However, approximately 15% of these subjects with hepatic fibrosis had nevirapine trough concentrations above 9,000 mcg per mL (2-fold the usual mean trough). Therefore, patients with hepatic impairment should be monitored carefully for evidence of drug-induced toxicity [see Warnings and Precautions (5.1)] . The subjects studied were receiving antiretroviral therapy containing nevirapine 200 mg twice daily for at least 6 weeks prior to pharmacokinetic sampling, with a median duration of therapy of 3.4 years.

In a pharmacokinetic trial where HIV-1 negative cirrhotic subjects with mild (Child-Pugh A; n=6) or moderate (Child-Pugh B; n=4) hepatic impairment received a single 200 mg dose of nevirapine, a significant increase in the AUC of nevirapine was observed in one subject with Child-Pugh B and ascites suggesting that patients with worsening hepatic function and ascites may be at risk of accumulating nevirapine in the systemic circulation. Because nevirapine induces its own metabolism with multiple dosing, this single-dose trial may not reflect the impact of hepatic impairment on multiple-dose pharmacokinetics.

Do not administer nevirapine to patients with moderate or severe (Child-Pugh Class B or C, respectively) hepatic impairment [see Contraindications (4), Warnings and Precautions (5.1), and Use in Specific Populations (8.7)] .

Gender

In the multinational 2NN trial, a population pharmacokinetic substudy of 1077 subjects was performed that included 391 females. Female subjects showed a 13.8% lower clearance of nevirapine than did men. Since neither body weight nor Body Mass Index (BMI) had an influence on the clearance of nevirapine, the effect of gender cannot solely be explained by body size.

Race

An evaluation of nevirapine plasma concentrations (pooled data from several clinical trials) from HIV-1-infected subjects (27 Black, 24 Hispanic, 189 Caucasian) revealed no marked difference in nevirapine steady-state trough concentrations (median Cminss= 4.7 mcg/mL Black, 3.8 mcg/mL Hispanic, 4.3 mcg/mL Caucasian) with long-term nevirapine treatment at 400 mg per day. However, the pharmacokinetics of nevirapine have not been evaluated specifically for the effects of ethnicity.

Black subjects (n=80/group) in Trial 1100.1486 showed approximately 30% to 35% higher trough concentrations than Caucasian subjects (250 to 325 subjects/group) in both immediate-release nevirapine and nevirapine extended-release tablets treatment groups over 96 weeks of treatment at 400 mg per day.

Geriatric Patients

Nevirapine pharmacokinetics in HIV-1-infected adults do not appear to change with age (range 18 to 68 years); however, nevirapine has not been extensively evaluated in subjects beyond the age of 55 years [see Use in Specific Populations (8.5)] .

Pediatric Patients

Pharmacokinetic data for nevirapine have been derived from two sources: a 48-week pediatric trial in South Africa (BI Trial 1100.1368) involving 123 HIV-1 positive, antiretroviral-naïve subjects aged 3 months to 16 years; and a consolidated analysis of five Pediatric AIDS Clinical Trials Group (PACTG) protocols comprising 495 subjects aged 14 days to 19 years.

BI Trial 1100.1368 studied the safety, efficacy, and pharmacokinetics of a weight-based and a body surface area (BSA)-based dosing regimen of nevirapine. In the weight-based regimen, pediatric subjects up to 8 years of age received a dose of 4 mg/kg once daily for two weeks followed by 7 mg per kg twice daily thereafter. Subjects 8 years and older were dosed 4 mg/kg once daily for two weeks followed by 4 mg/kg twice daily thereafter. In the BSA regimen, all pediatric subjects received 150 mg/m^2once daily for two weeks followed by 150 mg/m^2twice daily thereafter [see Use in Specific Populations (8.4)and Adverse Reactions (6.1)] . Dosing of nevirapine at 150 mg/m^2BID (after a two-week lead-in of 150 mg/m^2QD) produced geometric mean or mean trough nevirapine concentrations between 4 to 6 mcg per mL (as targeted from adult data). In addition, the observed trough nevirapine concentrations were comparable between the two dosing regimens studied (BSA- and weight-based methods).

The consolidated analysis of Pediatric AIDS Clinical Trials Group (PACTG) protocols 245, 356, 366, 377, and 403 allowed for the evaluation of pediatric subjects less than 3 months of age (n=17). The plasma nevirapine concentrations observed were within the range observed in adults and the remainder of the pediatric population, but were more variable between subjects, particularly in the second month of age. For dose recommendations for pediatric patients [see Dosage and Administration (2.2)] .

Drug Interactions [see Drug Interactions (7)]

Nevirapine induces hepatic cytochrome P450 metabolic isoenzymes 3A and 2B6. Co-administration of nevirapine and drugs primarily metabolized by CYP3A or CYP2B6 may result in decreased plasma concentrations of these drugs and attenuate their therapeutic effects.

While primarily an inducer of cytochrome P450 3A and 2B6 enzymes, nevirapine may also inhibit this system. Among human hepatic cytochrome P450s, nevirapine was capable in vitroof inhibiting the 10-hydroxylation of (R)-warfarin (CYP3A). The estimated Ki for the inhibition of CYP3A was 270 micromolar, a concentration that is unlikely to be achieved in patients as the therapeutic range is less than 25 micromolar. Therefore, nevirapine may have minimal inhibitory effect on other substrates of CYP3A.

Nevirapine does not appear to affect the plasma concentrations of drugs that are substrates of other CYP450 enzyme systems, such as 1A2, 2D6, 2A6, 2E1, 2C9, or 2C19.

Table 5 (see below) contains the results of drug interaction trials performed with nevirapine and other drugs likely to be co-administered. The effects of nevirapine on the AUC, Cmax, and Cminof co-administered drugs are summarized.

Table 5 Drug Interactions: Changes in Pharmacokinetic Parameters for Co-administered Drug in the Presence of Nevirapine (All interaction trials were conducted in HIV-1 positive subjects)

Co-administered Drug | Dose of Co administered Drug | Dose Regimen of Nevirapine | n | % Change of Co-administered Drug Pharmacokinetic Parameters (90% CI)
Antiretrovirals |  |  |  | AUC | Cmax |  | Cmin
Atazanavir/Ritonavira,d | 300/100 mg QD day 4 to 13, then 400/100 mg QD, day 14 to 23 | 200 mg BID day 1 to 23. Subjects were treated with nevirapine prior to trial entry. | 23 | Atazanavir 300/100 mg ↓42 (↓52 to ↓29) | Atazanavir 300/100 mg ↓28 (↓40 to ↓14) |  | Atazanavir 300/100 mg ↓72 (↓80 to ↓60)
Atazanavir/Ritonavira,d | 300/100 mg QD day 4 to 13, then 400/100 mg QD, day 14 to 23 | 200 mg BID day 1 to 23. Subjects were treated with nevirapine prior to trial entry. | 23 | Atazanavir 400/100 mg ↓19 (↓35 to ↑2) | Atazanavir 400/100 mg ↑2 (↓15 to ↑24) |  | Atazanavir 400/100 mg ↓59 (↓73 to ↓40)
Darunavir/Ritonavire | 400/100 mg BID | 200 mg BID | 8 | ↑24 (↓3 to ↑57) | ↑40 (↑14 to↑73) |  | ↑2 (↓21 to ↑32)
Didanosine | 100 to 150 mg BID | 200 mg QD x 14 days; 200 mg BID x 14 days | 18 | ⇔ | ⇔ |  | §
Efavirenza | 600 mg QD | 200 mg QD x 14 days; 400 mg QD x 14 days | 17 | ↓28 (↓34 to ↓14) | ↓12 (↓23 to ↑1) |  | ↓32 (↓35 to ↓19)
Fosamprenavir | 1400 mg BID | 200 mg BID. Subjects were treated with nevirapine prior to trial entry. | 17 | ↓33 (↓45 to ↓20) | ↓25 (↓37 to ↓10) |  | ↓35 (↓50 to ↓15)
Fosamprenavir/Ritonavir | 700/100 mg BID | 200 mg BID. Subjects were treated with nevirapine prior to trial entry. | 17 | ↓11 (↓23 to ↑3) | ⇔ |  | ↓19 (↓32 to ↓4)
Indinavira | 800 mg q8H | 200 mg QD x 14 days; 200 mg BID x 14 days | 19 | ↓31 (↓39 to ↓22) | ↓15 (↓24 to ↓4) |  | ↓44 (↓53 to ↓33)
Lopinavira,b | 300/75 mg/m^2(lopinavir/ ritonavir)b | 7 mg/kg or 4 mg/kg QD x 2 weeks; BID x 1 week | 12, 15c | ↓22 (↓44 to ↑9) | ↓14 (↓36 to ↑16) |  | ↓55 (↓75 to ↓19)
Lopinavira | 400/100 mg BID (lopinavir/ ritonavir) | 200 mg QD x 14 days; 200 mg BID >1 year | 22, 19c | ↓27 (↓47 to ↓2) | ↓19 (↓38 to ↑5) |  | ↓51 (↓72 to ↓26)
Maravirocf | 300 mg SD | 200 mg BID | 8 | ↑1 (↓35 to ↑55) | ↑54 (↓6 to ↑151) |  | ⇔
Nelfinavira Nelfinavir-M8 metabolite | 750 mg TID | 200 mg QD x 14 days; 200 mg BID x 14 days | 23 | ⇔ | ⇔ |  | ↓32 (↓50 to ↑5)
Nelfinavira Nelfinavir-M8 metabolite | 750 mg TID | 200 mg QD x 14 days; 200 mg BID x 14 days | 23 | ↓62 (↓70 to ↓53) | ↓59 (↓68 to ↓48) |  | ↓66 (↓74 to ↓55)
Ritonavir | 600 mg BID | 200 mg QD x 14 days; 200 mg BID x 14 days | 18 | ⇔ | ⇔ |  | ⇔
Stavudine | 30 to 40 mg BID | 200 mg QD x 14 days; 200 mg BID x 14 days | 22 | ⇔ | ⇔ |  | §
Zalcitabine | 0.125 to 0.25 mg TID | 200 mg QD x 14 days; 200 mg BID x 14 days | 6 | ⇔ | ⇔ |  | §
Zidovudine | 100 to 200 mg TID | 200 mg QD x 14 days; 200 mg BID x 14 days | 11 | ↓28 (↓40 to ↓4) | ↓30 (↓51 to ↑14) |  | §
Other Medications |  |  |  | AUC | Cmax |  | Cmin
Clarithromycina Metabolite 14-OH-clarithromycin | 500 mg BID | 200 mg QD x 14 days; 200 mg BID x 14 days | 15 | ↓31 (↓38 to ↓24) | ↓23 (↓31 to ↓14) |  | ↓56 (↓70 to ↓36)
Clarithromycina Metabolite 14-OH-clarithromycin | 500 mg BID | 200 mg QD x 14 days; 200 mg BID x 14 days |  | ↑42 (↑16 to ↑73) | ↑47 (↑21 to ↑80) |  | ⇔
Ethinyl Estradiolaand Norethindronea | 0.035 mg (as Ortho- Novum®1/35) 1 mg (as Ortho-Novum®1/35) | 200 mg QD x 14 days; 200 mg BID x 14 days | 10 | ↓20 (↓33 to ↓3) | ⇔ |  | §
Ethinyl Estradiolaand Norethindronea | 0.035 mg (as Ortho- Novum®1/35) 1 mg (as Ortho-Novum®1/35) | 200 mg QD x 14 days; 200 mg BID x 14 days | 10 | ↓19 (↓30 to ↓7) | ↓16 (↓27 to ↓3) |  | §
Depomedroxy Progesterone Acetate | 150 mg every 3 months | 200 mg QD x 14 days; 200 mg BID x 14 days | 32 | ⇔ | ⇔ |  | ⇔
Fluconazole | 200 mg QD | 200 mg QD x 14 days; 200 mg BID x 14 days | 19 | ⇔ | ⇔ |  | ⇔
Ketoconazolea | 400 mg QD | 200 mg QD x 14 days; 200 mg BID x 14 days | 21 | ↓72 (↓80 to ↓60) | ↓44 (↓58 to ↓27) |  | §
Methadonea | Individual Subject Dosing | 200 mg QD x 14 days; 200 mg BID ≥7 days | 9 | In a controlled pharmacokinetic trial with 9 subjects receiving chronic methadone to whom steady-state nevirapine therapy was added, the clearance of methadone was increased by 3-fold, resulting in symptoms of withdrawal, requiring dose adjustments in 10 mg segments, in 7 of the 9 subjects. Methadone did not have any effect on nevirapine clearance.
Rifabutina Metabolite 25-O-desacetyl-rifabutin | 150 or 300 mg QD | 200 mg QD x 14 days; 200 mg BID x 14 days | 19 | ↑17 (↓2 to ↑40) |  | ↑28 (↑9 to ↑51) |  | ⇔
Rifabutina Metabolite 25-O-desacetyl-rifabutin | 150 or 300 mg QD | 200 mg QD x 14 days; 200 mg BID x 14 days | 19 | ↑24 (↓16 to ↑84) |  | ↑29 (↓2 to ↑68) |  | ↑22 (↓14 to ↑74)
Rifampina | 600 mg QD | 200 mg QD x 14 days; 200 mg BID x 14 days | 14 | ↑11 (↓4 to ↑28) |  | ⇔ |  | §

§ = Cminbelow detectable level of the assay

↑ = Increase, ↓ = Decrease, ⇔ =No Effect

aFor information regarding clinical recommendations, see Drug Interactions (7).

bPediatric subjects ranging in age from 6 months to 12 years.

cParallel group design; n for nevirapine +lopinavir/ritonavir, n for lopinavir/ritonavir alone.

dParallel group design; n=23 for atazanavir/ritonavir + nevirapine, n=22 for atazanavir/ritonavir without nevirapine. Changes in atazanavir PK are relative to atazanavir/ritonavir 300/100 mg alone.

eBased on between-trial comparison.

fBased on historical controls.

Because of the design of the drug interaction trials (addition of 28 days of nevirapine therapy to existing HIV-1 therapy), the effect of the concomitant drug on plasma nevirapine steady-state concentrations was estimated by comparison to historical controls.

Administration of rifampin had a clinically significant effect on nevirapine pharmacokinetics, decreasing AUC and Cmaxby greater than 50%. Administration of fluconazole resulted in an approximate 100% increase in nevirapine exposure, based on a comparison to historic data [see Drug Interactions (7)] . The effect of other drugs listed in Table 5 on nevirapine pharmacokinetics was not significant. No significant interaction was observed when tipranavir was co-administered with low-dose ritonavir and nevirapine.

12.4 Microbiology

Mechanism of Action

Nevirapine is a non-nucleoside reverse transcriptase inhibitor (NNRTI) of HIV-1. Nevirapine binds directly to reverse transcriptase (RT) and blocks the RNA- dependent and DNA-dependent DNA polymerase activities by causing a disruption of the enzyme's catalytic site. The activity of nevirapine does not compete with template or nucleoside triphosphates. HIV-2 RT and eukaryotic DNA polymerases (such as human DNA polymerases α, ß, γ, or δ) are not inhibited by nevirapine.

Antiviral Activity

The antiviral activity of nevirapine has been measured in a variety of cell lines including peripheral blood mononuclear cells, monocyte-derived macrophages, and lymphoblastoid cell lines. In an assay using human embryonic kidney 293 cells, the median EC50value (50% inhibitory concentration) of nevirapine was 90 nM against a panel of 2923 wild-type isolates of HIV-1 that were primarily (93%) clade B clinical isolates from the United States. The 99thpercentile EC50value was 470 nM in this trial. The median EC50value was 63 nM (range 14 to 302 nM, n=29) against clinical isolates of HIV-1 clades A, B, C, D, F, G, and H, and circulating recombinant forms CRF01_AE, CRF02_AG and CRF12_BF. Nevirapine had no antiviral activity in cell culture against group O HIV-1 isolates (n=3) or HIV-2 isolates (n=3) replicating in cord blood mononuclear cells. Nevirapine in combination with efavirenz exhibited strong antagonistic anti-HIV-1 activity in cell culture and was additive to antagonistic with the protease inhibitor ritonavir or the fusion inhibitor enfuvirtide. The anti-HIV-1 activity of nevirapine was not antagonistic in combination with the NRTIs abacavir, didanosine, emtricitabine, lamivudine, stavudine, tenofovir and zidovudine, and the protease inhibitors amprenavir, atazanavir, indinavir, lopinavir, nelfinavir, saquinavir and tipranavir. The anti-HIV-1 activity of nevirapine was antagonized by the anti-HBV drug adefovir and by the anti-HCV drug ribavirin in cell culture.

Resistance

HIV-1 isolates with reduced susceptibility (100- to 250-fold) to nevirapine emerge in cell culture. Genotypic analysis showed mutations in the HIV-1 RT gene encoding Y181C and/or V106A substitutions depending upon the virus strain and cell line employed. Time to emergence of nevirapine resistance in cell culture was not altered when selection included nevirapine in combination with several other NNRTIs.

Phenotypic and genotypic changes in HIV-1 isolates from treatment-naïve subjects receiving either nevirapine (n=24) or nevirapine and zidovudine (n=14) were monitored in Phase 1 and 2 trials ranging from 1 to 12 weeks or longer. After 1 week of nevirapine monotherapy, isolates from 3/3 subjects had decreased susceptibility to nevirapine in cell culture. One or more of the RT mutations resulting in amino acid substitutions K103N, V106A, V108I, Y181C, Y188C, and G190A were detected in HIV-1 isolates from some subjects as early as 2 weeks after therapy initiation. By week eight of nevirapine monotherapy, 100% of the subjects tested (n=24) had HIV-1 isolates with a greater than 100-fold decrease in susceptibility to nevirapine in cell culture compared to baseline and had one or more of the nevirapine RT resistance-associated substitutions. Nineteen of these subjects (80%) had isolates with Y181C substitutions regardless of dose.

Genotypic analysis of isolates from antiretroviral-naïve subjects experiencing virologic failure (n=71) receiving nevirapine once daily (n=25) or twice daily (n=46) in combination with lamivudine and stavudine (trial 2NN) for 48 weeks showed that isolates from 8/25 and 23/46 subjects, respectively, contained one or more of the following NNRTI resistance-associated substitutions: Y181C, K101E, G190A/S, K103N, V106A/M, V108I, Y188C/L, A98G, F227L, and M230L.

For trial 1100.1486, genotypic analysis was performed for baseline and on-therapy isolates from 23 and 34 subjects who experienced virologic failure in the nevirapine extended-release and immediate-release nevirapine treatment group, respectively. Nevirapine resistance-associated substitutions developed in the on-therapy isolates of 78% (18/23) of the subjects who had virologic failures in the nevirapine extended-release treatment group and 88% (30/34) of the subjects in the immediate-release nevirapine treatment group, respectively. The Y181C nevirapine resistance-associated substitution was found alone or in combination with other nevirapine resistance-associated substitutions (K101E, K103N, V106A, V108I, V179D/E/I, Y188 C/F/H/L/N, G190A, P225H, F227L, M230L) in isolates from 14 subjects failing nevirapine extended-release tablets treatment and 25 subjects failing immediate-release nevirapine treatment. On-therapy isolates from 1 subject in nevirapine extended-release tablets treatment group developed a novel amino acid substitution Y181I and isolates from another subject in the immediate-release nevirapine treatment group developed a novel amino acid substitution Y188N. Phenotypic analysis showed that Y188N and Y181I substitutions conferred 103- and 22-fold reductions in susceptibility to nevirapine, respectively.

Cross-resistance

Rapid emergence of HIV-1 strains which are cross-resistant to NNRTIs has been observed in cell culture. Nevirapine-resistant HIV-1 isolates were cross-resistant to the NNRTIs efavirenz and etravirine. The Y188N conferred a 7-fold reduction in susceptibility to efavirenz but showed no decrease in susceptibility to etravirine. Similarly, the Y181I substitution reduced susceptibility to etravirine 8-fold, but did not reduce susceptibility to efavirenz. However, nevirapine-resistant isolates were susceptible to the NRTI ZDV. Similarly, ZDV-resistant isolates were susceptible to nevirapine in cell culture.

13 NONCLINICAL TOXICOLOGY

13.1 Carcinogenesis, Mutagenesis, Impairment of Fertility

Carcinogenesis
Long -term carcinogenicity studies in mice and rats were carried out with nevirapine. Mice were dosed with 0, 50, 375 or 750 mg/kg/day for two years. Hepatocellular adenomas and carcinomas were increased at all doses in males and at the two high doses in females. In studies in which rats were administered nevirapine at doses of 0, 3.5, 17.5 or 35 mg/kg/day for two years, an increase in hepatocellular adenomas was seen in males at all doses and in females at the high dose. The systemic exposure (based on AUCs) at all doses in the two animal studies was lower than that measured in humans at the 200 mg twice daily dose. The mechanism of the carcinogenic potential is unknown.

Mutagenesis

However, in genetic toxicology assays, nevirapine showed no evidence of mutagenic or clastogenic activity in a battery of in vitroand in vivostudies. These included microbial assays for gene mutation (Ames: Salmonella strains and E. coli), mammalian cell gene mutation assay (CHO/HGPRT), cytogenetic assays using a Chinese hamster ovary cell line and a mouse bone marrow micronucleus assay following oral administration. Given the lack of genotoxic activity of nevirapine, the relevance to humans of hepatocellular neoplasms in nevirapine-treated mice and rats is not known.

Impairment of Fertility

In reproductive toxicology studies, evidence of impaired fertility was seen in female rats at doses providing systemic exposure, based on AUC, approximately equivalent to that provided with the recommended clinical dose of nevirapine.

13.2 Animal Toxicology and/or Pharmacology

Animal studies have shown that nevirapine is widely distributed to nearly all tissues and readily crosses the blood-brain barrier.

14 CLINICAL STUDIES

14.1 Adult Patients

Trial BI 1090 was a placebo-controlled, double-blind, randomized trial in 2249 HIV-1 infected subjects with less than 200 CD4^+cells/mm^3at screening. Initiated in 1995, BI 1090 compared treatment with nevirapine + lamivudine + background therapy versus lamivudine + background therapy in NNRTI-naïve subjects. Treatment doses were nevirapine, 200 mg daily for two weeks followed by 200 mg twice daily or placebo, and lamivudine, 150 mg twice daily. Other antiretroviral agents were given at approved doses. Initial background therapy (in addition to lamivudine) was one NRTI in 1309 subjects (58%), two or more NRTIs in 771 (34%), and PIs and NRTIs in 169 (8%). The subjects (median age 36.5 years, 70% Caucasian, 79% male) had advanced HIV-1 infection, with a median baseline CD4^+cell count of 96 cells/mm^3and a baseline HIV-1 RNA of 4.58 log10 copies per mL (38,291 copies per mL). Prior to entering the trial, 45% had previously experienced an AIDS-defining clinical event. Eighty-nine percent had antiretroviral treatment prior to entering the trial. BI 1090 was originally designed as a clinical endpoint trial. Prior to unblinding the trial, the primary endpoint was changed to proportion of subjects with HIV-1 RNA less than 50 copies per mL and not previously failed at 48 weeks. Treatment response and outcomes are shown in Table 6.

Table 6 BI 1090 Outcomes Through 48 Weeks

Outcome | Nevirapine (N=1121) % | Placebo (N=1128) %
Responders at 48 weeks: HIV-1 RNA <50 copies/mL | 18 | 2
Treatment Failure | 82 | 98
Never suppressed viral load | 45 | 66
Virologic failure after response | 7 | 4
CDC category C event or death | 10 | 11
Added antiretroviral therapy^1while <50 copies/mL | 5 | 1
Discontinued trial therapy due to AE | 7 | 6
Discontinued trial <48 weeks^2 | 9 | 10

^1including change to open-label nevirapine

^2includes withdrawal of consent, lost to follow-up, non-compliance with protocol, other administrative reasons

The change from baseline in CD4^+cell count through one year of therapy was significantly greater for the nevirapine group compared to the placebo group for the overall trial population (64 cells/mm^3versus 22 cells/mm^3, respectively), as well as for subjects who entered the trial as treatment-naïve or having received only ZDV (85 cells/mm^3versus 25 cells/mm^3, respectively).

At two years into the trial, 16% of subjects on nevirapine had experienced class C CDC events as compared to 21% of subjects on the control arm.

Trial BI 1046 (INCAS) was a double-blind, placebo-controlled, randomized, three-arm trial with 151 HIV-1 infected subjects with CD4^+cell counts of 200 to 600 cells/mm^3at baseline. BI 1046 compared treatment with nevirapine +zidovudine+didanosine to nevirapine +zidovudine and zidovudine+didanosine. Treatment doses were nevirapine at 200 mg daily for two weeks followed by 200 mg twice daily or placebo, zidovudine at 200 mg three times daily, and didanosine at 125 or 200 mg twice daily (depending on body weight). The subjects had mean baseline HIV-1 RNA of 4.41 log10 copies/mL (25,704 copies per mL) and mean baseline CD4^+cell count of 376 cells/mm^3. The primary endpoint was the proportion of subjects with HIV-1 RNA less than 400 copies per mL and not previously failed at 48 weeks. The virologic responder rates at 48 weeks were 45% for subjects treated with nevirapine +zidovudine+didanosine, 19% for subjects treated with zidovudine+didanosine, and 0% for subjects treated with nevirapine +zidovudine.

CD4+ cell counts in the nevirapine +ZDV+ddI group increased above baseline by a mean of 139 cells/mm^3at one year, significantly greater than the increase of 87 cells/mm^3in the ZDV+ddI subjects. The nevirapine +ZDV group mean decreased by 6 cells/mm^3below baseline.

14.2 Pediatric Patients

The pediatric safety and efficacy of nevirapine was examined in BI Trial 1100.1368, an open-label, randomized clinical trial performed in South Africa in which 123 HIV-1 infected treatment-naïve subjects between 3 months and 16 years of age received for 48 weeks. Subjects were divided into 4 age groups (3 months to less than 2 years, 2 to less than 7 years, 7 to less than 12 years, and 12 to less than or equal to 16 years) and randomized to receive one of two nevirapine doses, determined by 2 different dosing methods [body surface area (150 mg/m^2) and weight-based dosing (4 or 7 mg per kg)] in combination with zidovudine and lamivudine [see Adverse Reactions (6.1), Use in Specific Populations (8.4), and Clinical Pharmacology (12.3)] . The total daily dose of nevirapine did not exceed 400 mg in either regimen. There were 66 subjects in the body surface area (BSA) dosing group and 57 subjects in the weight-based (BW) dosing group.

Baseline demographics included: 49% male; 81% Black and 19% Caucasian; 4% had previous exposure to ARVs. Subjects had a median baseline HIV-1 RNA of 5.45 log10 copies per mL and a median baseline CD4^+cell count of 527 cells/mm^3(range 37 to 2279). One hundred and five (85%) completed the 48-week period while 18 (15%) discontinued prematurely. Of the subjects who discontinued prematurely, 9 (7%) discontinued due to adverse reactions and 3 (2%) discontinued due to virologic failure. Overall the proportion of subjects who achieved and maintained an HIV-1 RNA less than 400 copies per mL at 48 weeks was 47% (58/123).

16 HOW SUPPLIED/STORAGE AND HANDLING

Nevirapine Tablets USP, 200 mg are White to off-white, oval, biconvex tablet, marked on one side as “I” and “11” separated with a breakline and plain on other side.

Pack style: Blister Pack of 60 (6 x 10) Unit-dose Tablets

Packing configuration: 10 Tablets packed in a Blister and such 6 Blister are packed in one Carton

(NDC code: 42571-131-29).

Pack style: HDPE Bottle pack of 60s Tablets (NDC code: 42571-131-60).

Dispense in tight container as defined in the USP/NF.

Storage

Store at 25°C (77°F); excursions permitted to 15°C to 30°C (59°F to 86°F)[see USP Controlled Room Temperature]. Store in a safe place out of the reach of children.

17 PATIENT COUNSELING INFORMATION

Advise the patient to read the FDA-approved patient labeling (Medication Guide).

Hepatotoxicity and Skin Reactions

Inform patients of the possibility of severe liver disease or skin reactions associated with nevirapine that may result in death. Instruct patients developing signs or symptoms of liver disease or severe skin reactions to discontinue nevirapine and seek medical attention immediately, including performance of laboratory monitoring. Symptoms of liver disease include fatigue, malaise, anorexia, nausea, jaundice, acholic stools, liver tenderness or hepatomegaly. Symptoms of severe skin or hypersensitivity reactions include rash accompanied by fever, general malaise, fatigue, muscle or joint aches, blisters, oral lesions, conjunctivitis, facial edema, and/or hepatitis.

Intensive clinical and laboratory monitoring, including liver enzymes, is essential during the first 18 weeks of therapy with nevirapine to detect potentially life- threatening hepatotoxicity and skin reactions. However, liver disease can occur after this period; therefore, monitoring should continue at frequent intervals throughout nevirapine treatment. Extra vigilance is warranted during the first 6 weeks of therapy, which is the period of greatest risk of hepatic events. Advise patients with signs and symptoms of hepatitis to discontinue nevirapine and seek medical evaluation immediately. If nevirapine is discontinued due to hepatotoxicity, do not restart it. Patients, particularly women, with increased CD4^+cell count at initiation of nevirapine therapy (greater than 250 cells/mm^3in women and greater than 400 cells/mm^3in men) are at substantially higher risk for development of symptomatic hepatic events, often associated with rash. Advise patients that co-infection with hepatitis B or C and/or increased transaminases at the start of therapy with nevirapine are associated with a greater risk of later symptomatic events (6 weeks or more after starting nevirapine) and asymptomatic increases in AST or ALT [see Warnings and Precautions (5.1)] .

The majority of rashes associated with nevirapine occur within the first 6 weeks of initiation of therapy. Instruct patients that if any rash occurs during the two-week lead-in period, do not escalate the nevirapine dose until the rash resolves. The total duration of the once-daily lead-in dosing period should not exceed 28 days, at which point an alternative regimen may need to be started. Any patient experiencing a rash should have their liver enzymes (AST, ALT) evaluated immediately. Patients with severe rash or hypersensitivity reactions should discontinue nevirapine immediately and consult a physician. Nevirapine should not be restarted following severe skin rash or hypersensitivity reaction. Women tend to be at higher risk for development of nevirapine-associated rash [see Warnings and Precautions (5.2)] .

Administration and Missed Dosage

Inform patients to take nevirapine every day as prescribed. Advise patients not to alter the dose without consulting their doctor. If a dose is missed, patients should take the next dose as soon as possible. However, if a dose is skipped, the patient should not double the next dose.

To avoid overdose, inform patients that they should never take immediate-release nevirapine and nevirapine extended-release concomitantly.

Drug Interactions

Nevirapine may interact with some drugs; therefore, advise patients to report to their doctor the use of any other prescription, non-prescription medication or herbal products, particularly St. John's wort [see Warnings and Precautions (5.4)and Drug Interactions (7)] .

Immune Reconstitution Syndrome

Advise patients to inform their healthcare provider immediately of any signs or symptoms of infection, as inflammation from previous infection may occur soon after combination antiretroviral therapy, including when nevirapine is started [see Warnings and Precautions (5.5)].

Fat Redistribution

Inform patients that redistribution or accumulation of body fat may occur in patients receiving antiretroviral therapy and that the cause and long-term health effects of these conditions are not known at this time [see Warnings and Precautions (5.6)] .

Pregnancy Registry

Advise patients that there is a pregnancy registry that monitors pregnancy outcomes in women exposed to nevirapine during pregnancy [see Use in Specific Populations (8.1)].

Lactation

Instruct women with HIV-1 infection not to breastfeed because HIV-1 can be passed to the baby in the breast milk [see Use in Specific Populations (8.2)] .

Infertility

Advise females of reproductive potential of the potential for impaired fertility from nevirapine [see Use in Specific Populations (8.3)and Nonclinical Toxicology (13.1)]

Manufactured by:
Micro Labs Limited
Goa-403 722, INDIA.

Manufactured for:
Micro Labs USA, Inc.
Somerset, NJ 08873

Rev. 06/2022

MEDICATION GUIDE

Nevirapine (ne-VIR-a-peen) tablets, USP

What is the most important information I should know aboutnevirapine?

Nevirapine tabletscan cause severe liver and skin problems that may lead to death. These problems can happen at any time during treatment, but your risk is higher during the first 18 weeks of treatment.

Nevirapine can cause serious side effects, including:

- Severe liver problems.Some people taking nevirapine tablets may develop severe liver problems that can lead to liver failure and the need for a liver transplant, or death. If you have liver problems, you may get a rash.

- Women have a higher risk of developing liver problems during treatment with nevirapine than men.
- People who have abnormal liver test results before starting nevirapine and people with hepatitis B or C also have a greater risk of getting liver problems.

People who have higher CD4^+cell counts when they begin nevirapine have a higher risk of liver problems, especially:

- Women with CD4^+counts higher than 250 cells/mm^3. This group has the highest risk.
- Men with CD4^+counts higher than 400 cells/mm^3.

Stop takingnevirapineand call your doctor right away if you have any of the following symptoms of liver problems with or without a skin rash:

- dark (tea colored) urine

- yellowing of your skin or whites of your eyes

- light-colored bowel movements (stools)

- fever

- feeling sick to your stomach (nausea)

- feel unwell or like you have the flu

- pain or tenderness on your right side below your ribs

- tiredness

- loss of appetite

- Severe skin reactions and rash.Some skin reactions and rashes may be severe, life-threatening, and in some people, may lead to death. Most severe skin reactions and rashes happen in the first 6 weeks of treatment with nevirapine tablets.

- Women have a higher risk of developing a rash during treatment with nevirapine than men.

Stop takingnevirapineand call your doctor right away if you get a rash with any of the following symptoms:

- blisters

- muscle or joint aches

- red or inflamed eyes, like “pink eye” (conjunctivitis)

- mouth sores

- swelling of your face

- fever

- feel unwell or like you have the flu

- tiredness

- Your doctor should do blood tests often to check your liver function and check for severe skin reactions during the first 18 weeks of treatment with nevirapine. You should continue to see your doctor and have your liver checked regularly during your treatment with nevirapine tablets. It is important for you to keep all of your doctor appointments.
- If your doctor tells you to stop treatment withnevirapinebecause you have had any of the severe liver or skin symptoms listed above, you should never take nevirapine again.

See "What are the possible side effects ofnevirapine tablets?" for more information about side effects.

What arenevirapine tablets?

Nevirapine tablets are prescription HIV-1 medicines used with other HIV-1 medicines to treat HIV-1 (Human Immunodeficiency Virus 1) in adults and in children 15 days of age or older. HIV-1 is the virus that causes AIDS (Acquired Immune Deficiency Syndrome).

- If you are a woman with CD4^+counts higher than 250 cells/mm^3or a man with CD4^+counts higher than 400 cells/mm^3, you and your doctor will decide if starting nevirapine tablet is right for you.
- Nevirapine extended-release tablets are not recommended for use in children less than 6 years of age.

Do not takenevirapine:

- if you have liver problems.
- as part of occupational and non-occupational post-exposure prophylaxis (PEP) regimens. Nevirapine tablet is only for people diagnosed with HIV-1. If you have not been diagnosed as HIV positive, then do not take nevirapine tablets.

Before takingnevirapine, tell your doctor about all your or your child’s medical conditions, including if you or your child:

- have or have had hepatitis (inflammation of your liver) or problems with your liver. See “What is the most important information I should know aboutnevirapine?”
- receive dialysis
- have trouble swallowing pills
- are pregnant or plan to become pregnant. It is not known if nevirapine will harm your unborn baby.

Pregnancy Registry:There is a pregnancy registry for women who take nevirapine during pregnancy. The purpose of the registry is to collect information about the health of you and your baby. Talk to your doctor about how you can take part in this registry.

- are breastfeeding or plan to breastfeed. Nevirapine can pass into your breast milk and may harm your baby. You should not breastfeed if you have HIV-1 because of the risk of passing HIV-1 to your baby. Do not breastfeed during treatment with nevirapine. Talk to your doctor about the best way to feed your baby.

Tell your doctor about all the medicines you take,including prescription and over-the-counter medicines, vitamins and herbal supplements. Especially tell your doctor if you take St. John’s wort.

- Some medicines interact with nevirapine tablets. Keep a list of your medicines to show your doctor or pharmacist.
- You can ask your doctor or pharmacist for a list of medicines that interact with nevirapine tablets.
- Do not start taking a new medicine without telling your doctor. Your doctor can tell you if it is safe to take nevirapine tablets with other medicines.

How should I takenevirapine?

- Take nevirapine exactly as your doctor tells you to take it. Do not change your dose unless your doctor tells you to.
- Nevirapine tablet is always taken in combination with other antiretroviral medicines.
- Nevirapine tablet comes in three different forms. Your doctor will prescribe the form of nevirapine that is right for you.

- Nevirapine tablets
- Nevirapine oral suspension
- Nevirapine extended-release tablets

- You should not take more than one form of nevirapine tablets at the same time. Talk to your doctor if you have any questions.
- If your child is prescribed nevirapine, your child’s doctor will tell you exactly how nevirapine should be taken.
- Nevirapine can be taken with or without food.
- Swallow nevirapine extended-release tablets whole. Do not chew, crush, or divide nevirapine extended-release tablets.
- Do not miss a dose of nevirapine tablets?”. If you miss a dose of nevirapine tablets, take the missed dose as soon as you remember. If it is almost time for your next dose, do not take the missed dose. You should take the next dose at your regular time. Do not take 2 doses at the same time.
- If you stop taking nevirapine tablets for more than 7 days, ask your doctor how much to take before you start taking it again. You may need to begin taking the nevirapine tablets starting dose again, which is taken 1 time each day for 14 days.

Startingnevirapinetablets:

1. Your doctor should start you with 1 dose each day to lower your chance of getting a serious rash . It is important that you only take 1 dose ofnevirapineeach day for the first 14 days.

- Call your doctor right away if you get a skin rash during the first 14 days ofnevirapinetreatment.
- Do not increase your dose to 2 times a day if you have a rash.
- You should never take your starting dose for longer than 28 days. If after 28 days you are still receiving this starting dose because you have a rash, you and your doctor should talk about prescribing another HIV-1 medicine for you instead of nevirapine.

2. Day 15, you will take 1 nevirapine tablet 2 times a day.

Startingnevirapine extended-release tablets when this is the first time you are taking any form of nevirapine:

1. Your doctor should start you with 1 dose of nevirapine tablets each day to lower your risk of getting a serious rash. It is important that you only take 1 dose ofnevirapine each day for the first 14 days.

- Call your doctor right away if you get a skin rash during the first 14 days of nevirapine treatment.
- You should never take your starting dose for longer than 28 days. If after 28 days you are still receiving this starting dose because you have a rash, you and your doctor should talk about prescribing another HIV-1 medicine for you instead of nevirapine tablets.
- Do not startnevirapine extended-release tablets if you have a rash.

2. Day 15, take nevirapine extended-release tablets 1 time a day as prescribed by your doctor.

Switching from nevirapine tablets to nevirapine extended-release tablets:

- Take nevirapine extended-release tablets 1 time a day as prescribed by your doctor.
- You may sometimes pass a soft mass in your stools (bowel movement) that looks like your nevirapine extended-release tablets. This will not affect the way your medicine works.

What are the possible side effects ofnevirapine?

Nevirapine may cause serious side effects, including:

See " What is the most important information I should know aboutnevirapine?"

- Changes in your immune system (Immune Reconstitution Syndrome)can happen when you start taking HIV-1 medicines. Your immune system may get stronger and begin to fight infections that have been hidden in your body for a long time. Tell your doctor right away if you start having new symptoms after starting your HIV-1 medicine.
- Changes in body fatcan happen in people who take HIV-1 medicines. These changes may include increased amount of fat in the upper back and neck (“buffalo hump”), breast, and around the middle of your body (trunk). Loss of fat from your legs, arms, and face may also happen. The exact cause and long-term health effects of these conditions are not known.

The most common side effect ofnevirapineis rash.

Nevirapine may cause decreased fertility in females. Talk to your doctor if you have concerns about fertility.

These are not all the possible side effects of nevirapine. For more information, ask your doctor or pharmacist.

Call your doctor for medical advice about side effects. You may report side effects to FDA at 1-800-FDA-1088.

How should I storenevirapine?

- Store nevirapine at room temperature between 68°F to 77°F (20°C to 25°C).

Keepnevirapineand all medicines out of the reach of children.

General information about the safe and effective use ofnevirapine.

Medicines are sometimes prescribed for purposes other than those listed in a Medication Guide. Do not use nevirapine for a condition for which it was not prescribed. Do not give nevirapine tablets to other people, even if they have the same condition you have. It may harm them. You can ask your pharmacist or doctor for information about nevirapine tablets that is written for health professionals.

For more information, call Micro Labs USA Inc. at 1-855-839-8195.

What are the ingredients innevirapine tablets?

Active ingredient:Nevirapine Anhydrous

Inactive ingredients:

Nevirapine tablets:microcrystalline cellulose, lactose monohydrate, colloidal silicon dioxide, magnesium stearate, povidone, and Sodium starch glycolate.

This Medication Guide has been approved by the U.S. Food and Drug Administration

Manufactured by:
Micro Labs Limited
Goa-403 722, INDIA.

Manufactured for:
Micro Labs USA, Inc.
Somerset, NJ 08873

Rev. 06/2022

PACKAGE LABEL.PRINCIPAL DISPLAY PANEL

NDC 42571-131-60
Rx Only
Nevirapine
Tablets, USP
200 mg
Pharmacist: Dispense the accompanying
medication guide with the drug product.
60 TABLETS

Micro Labs Limited